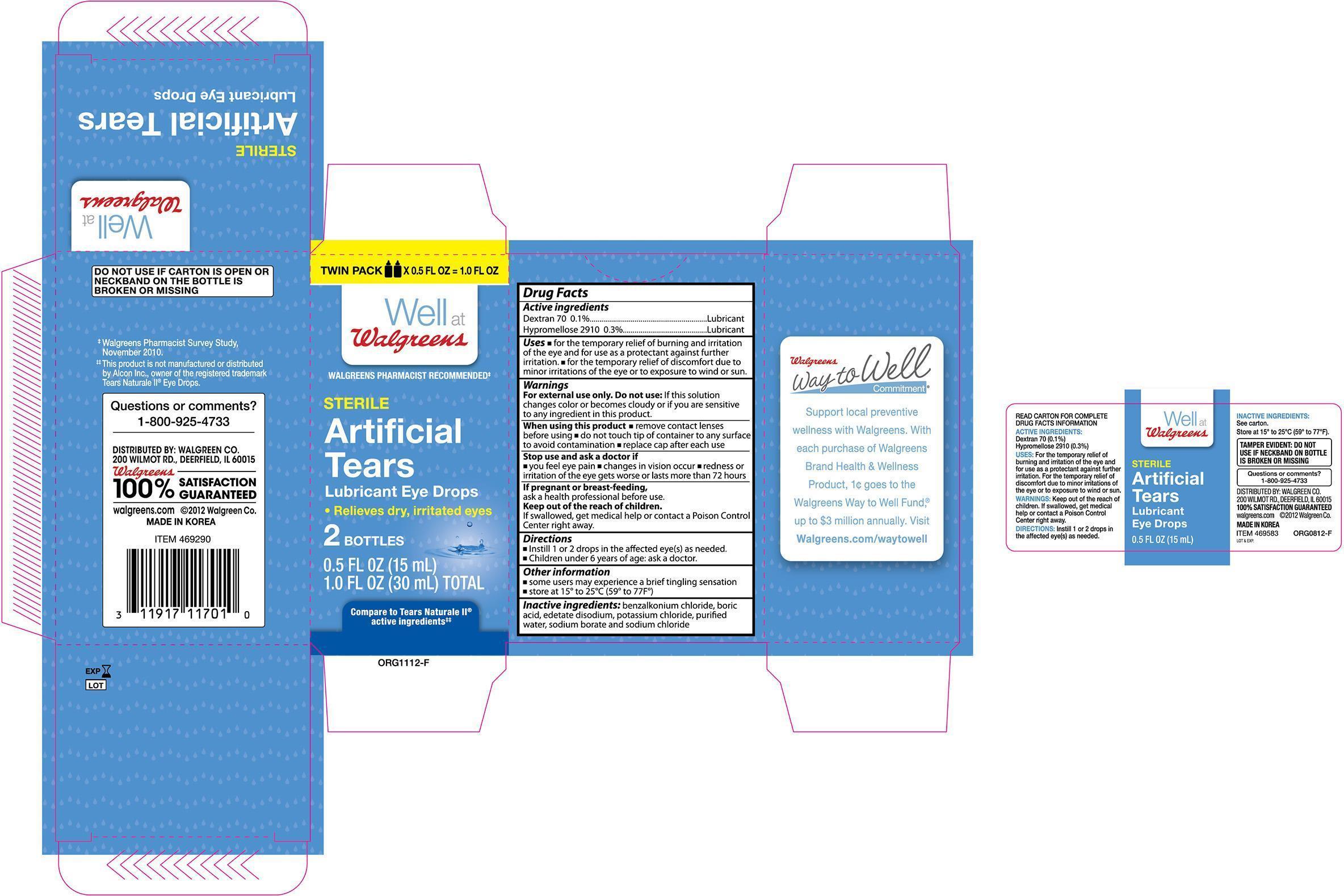 DRUG LABEL: Walgreens Artificial Tears Lubricant Eye Drops
NDC: 0363-1701 | Form: SOLUTION/ DROPS
Manufacturer: Walgreens Company
Category: otc | Type: HUMAN OTC DRUG LABEL
Date: 20131002

ACTIVE INGREDIENTS: DEXTRAN 70 .001 mg/1 mg; HYPROMELLOSES .003 mg/1 mg
INACTIVE INGREDIENTS: BENZALKONIUM CHLORIDE; BORIC ACID; EDETATE DISODIUM; POTASSIUM CHLORIDE; WATER; SODIUM BORATE; SODIUM CHLORIDE

Drug Facts

Active Ingredients

Dextran 70 0.1%..................................... Lubricant

Hypromellose 2910 0.3%.......................... Lubricant

Uses

- for the temporary relief of burning and irritation of the eye and for use as a protectant against further irritation
- for the temporary relief of discomfort due to minor irritations of the eye or to exposure to wind or sun.

Warnings

For external use only. Do not use: if this solution changes color or becomes cloudy or if you are sensitive to any ingredient in this product.

When using this product

- remove contact lenses before using
- do not touch tip of container to any surface to avoid contamination
- replace cap after each use

Stop use and ask a doctor if

- you feel eye pain
- changes in vision occur
- redness or irritation of the eye gets worse or lasts more than 72 hours

If pregnant or breast-feeding

ask a health professional before use.

Keep out of the reach of children.

If swallowed, get medical help or contact a Poision Control Center right away.

Directions

- Instill 1 or 2 drops in the affected eye(s) as needed.
- Children under 6 years of age: ask a doctor.

Other Information

- some users may experience a brief tingling sensation
- store at 15° to 25°C (59° to 77°F)

INACTIVE INGREDIENT

Inactive Ingredients: benzalkonium chloride, boric acid, edetate disodium, potassium chloride, purified water, sodium borate, and sodium chloride

DOSAGE AND ADMINISTRATION

DISTRIBUTED BY:

WALGREEN CO.

200 WILMOT RD.

DEERFIELD, IL 60015